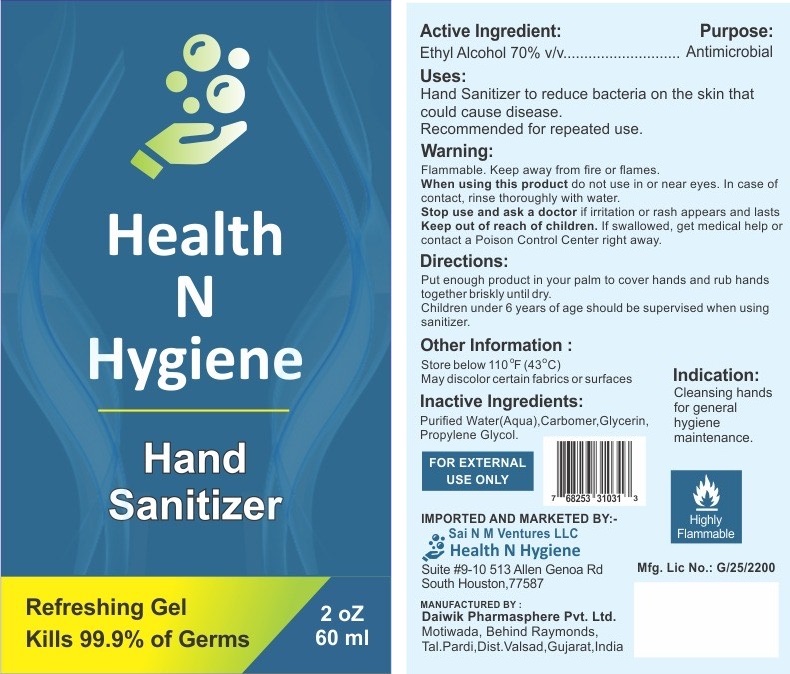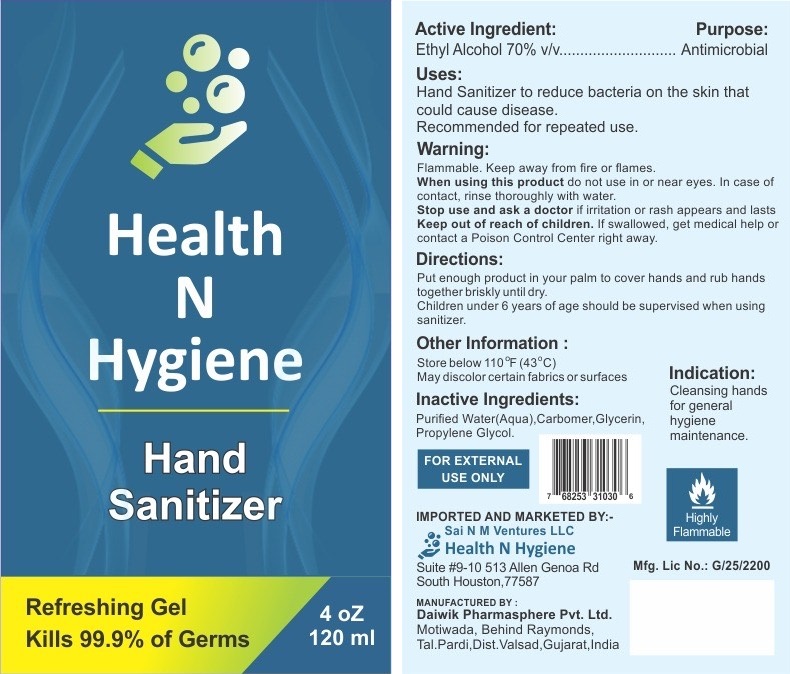 DRUG LABEL: Health N Hygiene Hand Sanitizer
NDC: 80198-001 | Form: GEL
Manufacturer: Sai N.M. Ventures LLC
Category: otc | Type: HUMAN OTC DRUG LABEL
Date: 20201001

ACTIVE INGREDIENTS: ALCOHOL 0.7 mL/1 mL
INACTIVE INGREDIENTS: WATER; CARBOMER HOMOPOLYMER, UNSPECIFIED TYPE; GLYCERIN; PROPYLENE GLYCOL

Health N Hygiene Hand Sanitizer

Active Ingredient:

Ethyl Alcohol 70% v/v

Purpose:

Antimicrobial

Uses:

Hand Sanitizer to reduce bacteria on the skin that could cause disease.

Recommended for repeated use.

Warning:

Flammable. Keep away from fire or flames.

When using this product

do not use in or near eyes. In case of contact, rinse thoroughly with water.

Stop use and ask a doctor

if irritation or rash appears and lasts

Keep out of reach of children.

If swallowed, get medical help or contact a Poison Control Center right away.

Directions:

Put enough product in your palm to cover hands and rub hands together briskly until dry.

Children under 6 years of age should be supervised when using sanitizer.

Other Information:

Store below 110 °F (43°C)

May discolor certain fabrics or surfaces

Inactive Ingredients:

Purified Water(Aqua), Carbomer, Glycerin, Propylene Glycol.